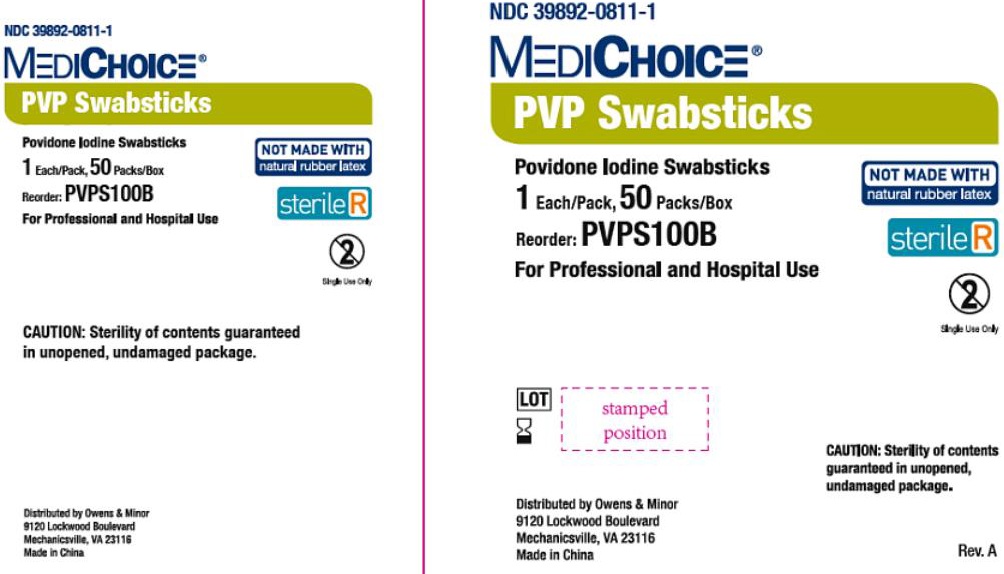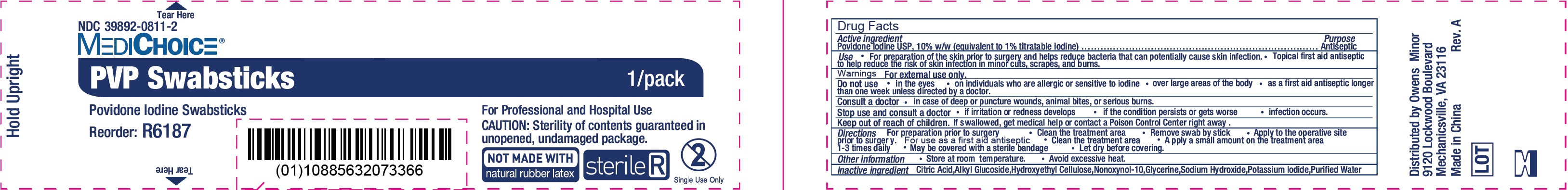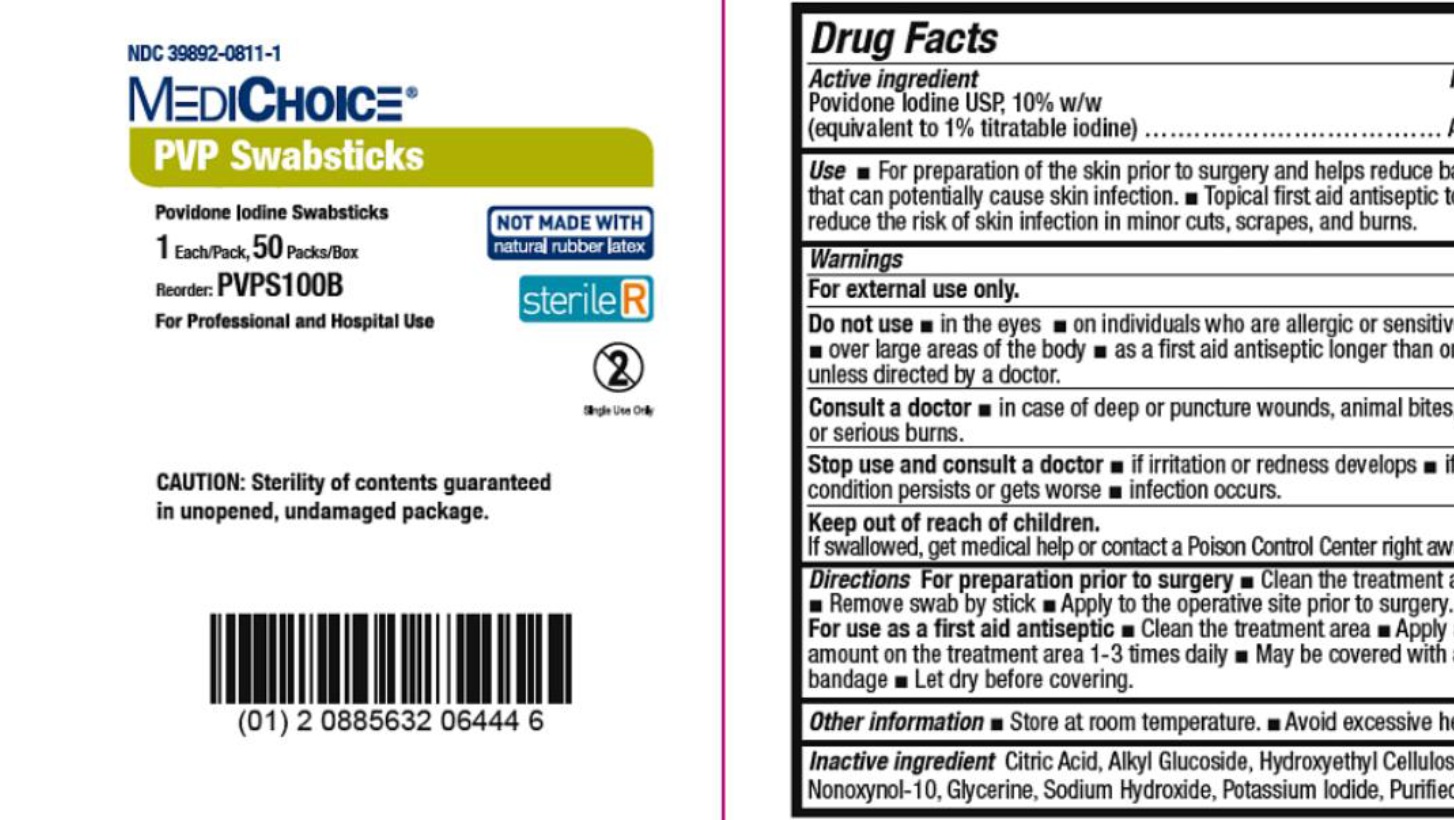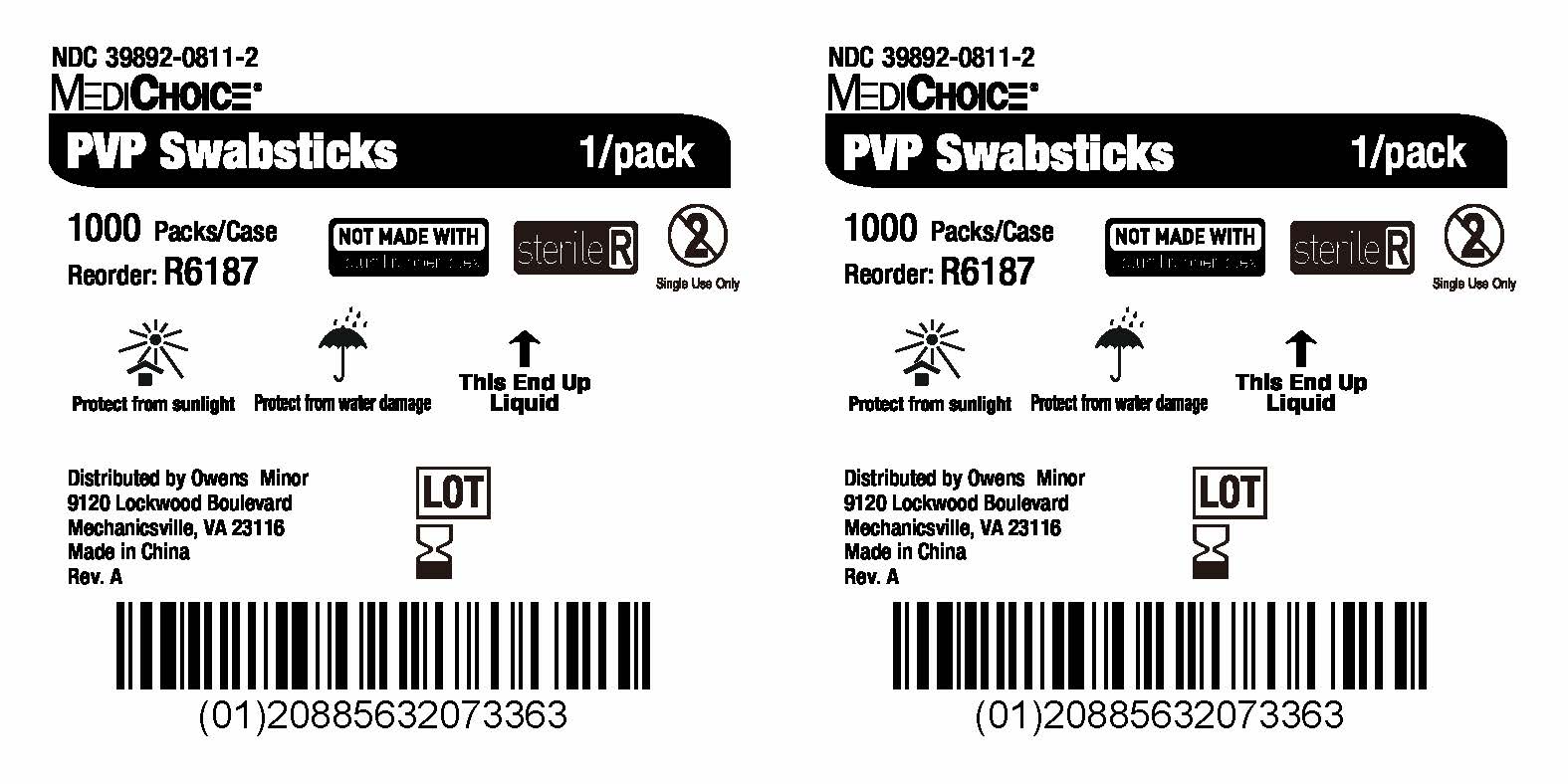 DRUG LABEL: MediChoice PVP
NDC: 39892-0811 | Form: SWAB
Manufacturer: O&M HALYARD, INC.
Category: otc | Type: HUMAN OTC DRUG LABEL
Date: 20251009

ACTIVE INGREDIENTS: POVIDONE-IODINE 10 g/100 g
INACTIVE INGREDIENTS: CITRIC ACID MONOHYDRATE; NONOXYNOL-10; GLYCERIN; SODIUM HYDROXIDE; POTASSIUM IODIDE; WATER

MediChoice PVP Swabsticks

Active ingredient

Povidone Iodine USP,10% w/w

Purpose

Antiseptic

Use

For preparation of the skin prior to surgery and helps reduce bacteria that can potentially cause skin infection. Topical first aid antiseptic to help reduce the risk of skin infection in minor cuts, scrapes, and burns.

Warnings

For external use only.

Do not use

- in the eyes
- on individuals who are allergic or sensitive to iodine
- over large areas of the body
- as a first aid antiseptic longer than one week unless directed by a doctor.

Consult a doctor

- in case of deep or puncture wounds, animal bites, or serious burns.

Stop use and consult a doctor

- if irritation or redness develops
- if the condition persists or gets worse
- infection occurs.

Keep out of reach of children.

If swallowed, get medical help or contact a Poison Control Center right away.

Directions

For preparation prior to surgery Clean the treatment area Remove swab by stick Apply to the operative site prior to surgery. Clean the treatment area Apply a small amount on the treatment area 1-3 times daily May be covered with a sterile bandage Let dry before covering.
For use as a first aid antiseptic

Other information

- Store at room temperature.
- Avoid excessive heat.

Inactive ingredient

Citric Acid, Alkyl Glucoside, Hydroxyethyl Cellulose, Nonoxyno-10, Glycerine, Sodium Hydroxide, Potassium Iodide, Purified Water